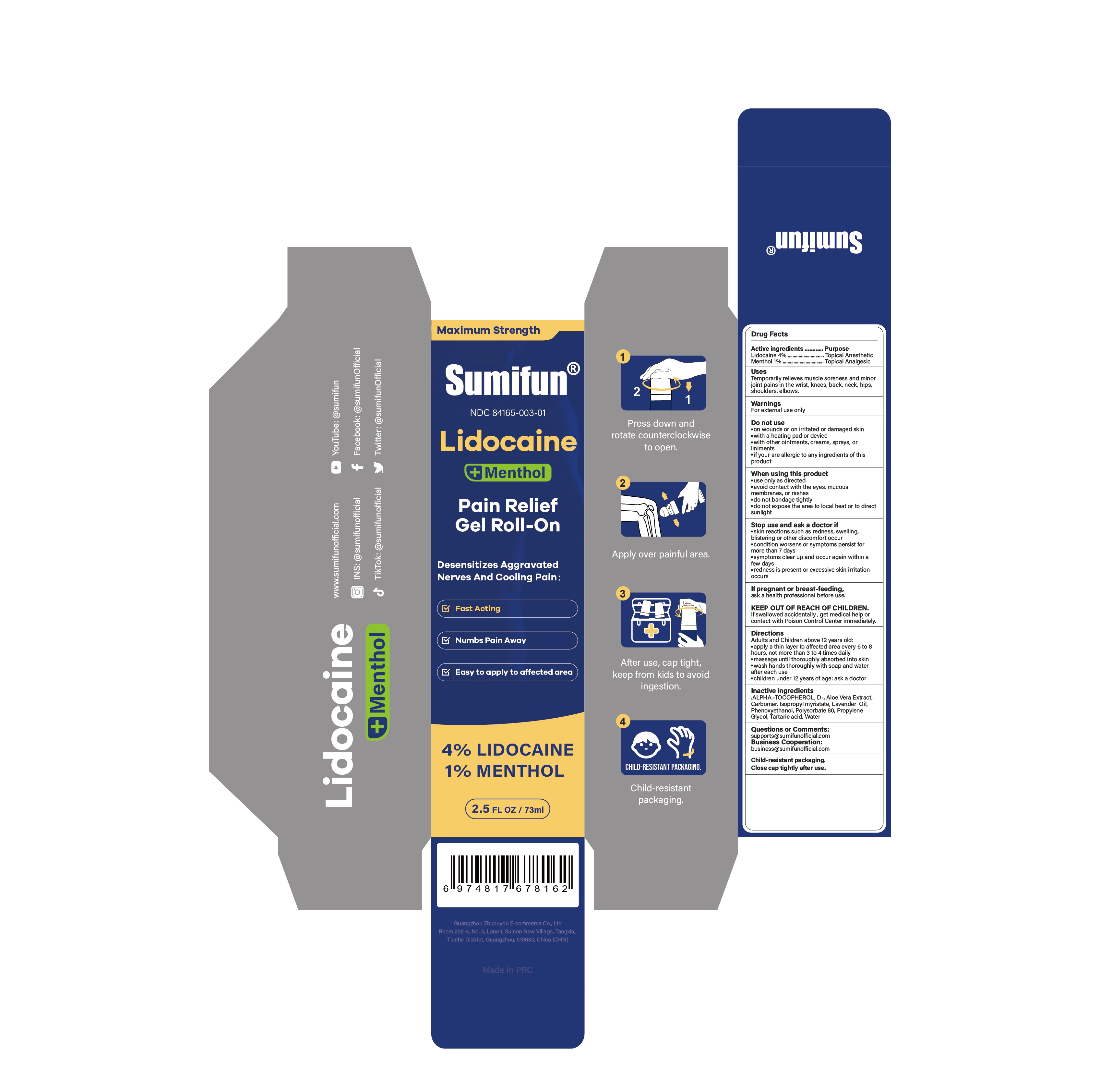 DRUG LABEL: Lidocaine Pain Relief Gel Roll-On
NDC: 84165-003 | Form: GEL
Manufacturer: Guangzhou Zhupuyou E-commerce Co., Ltd
Category: otc | Type: HUMAN OTC DRUG LABEL
Date: 20250810

ACTIVE INGREDIENTS: MENTHOL 0.01 g/1 mL; LIDOCAINE 0.04 g/1 mL
INACTIVE INGREDIENTS: ALOE VERA LEAF; LAVENDER OIL; POLYSORBATE 80; TARTARIC ACID; WATER; CARBOMER; PROPYLENE GLYCOL; .ALPHA.-TOCOPHEROL, D-; PHENOXYETHANOL; ISOPROPYL MYRISTATE

84165-003 Lidocaine Pain Relief Gel Roll-On

ACTIVE INGREDIENT

Lidocaine 4%
Menthol 1%

PURPOSE

Topical Anesthetic, Topical Analgesic

INDICATIONS AND USAGE

Temporarily relieves muscle soreness and minorjoin pains in the wrist,knees, back, neck, hips,shoulders,elbows.

WARNINGS

For external use only

DO NOT USE

on wounds or on irritated or damaged skin
with a heating pad or device
with other ointments,creams, sprays, orliniments
if your are allergic to any ingredients of this product

WHEN USING

use only as directed
avoid contact with the eyes, mucous membranes,or rashes
do not bandage tightly
do not expose the area to local heat or to direct sunlight

STOP USE

skin reactions such as redness,swelling blistering or other discomfort occur
condition worsens or symptoms persist formore than 7 days
symptoms clear up and occur again within afew days
redness is present or excessive skin irritation occurs

KEEP OUT OF REACH OF CHILDREN

lf swallowed accidentally ,get medical help orcontact with Poison Control Center immediately.

DOSAGE AND ADMINISTRATION

Adults and Children above 12 years old:
apply a thin layer to affected area every 6 to 8 hours, not more than 3 to 4 times daily
massage until thoroughly absorbed into skin
wash hands thoroughly with soap and waterafter each use
children under 12 years of age: ask a doctor

INACTIVE INGREDIENT

.ALPHA.-TOCOPHEROL, D-
Aloe Vera Extract
Carbomer
Isopropyl myristate
Lavender Oil
Phenoxyethanol
Polysorbate 80
Propylene Glycol
Tartaric acid
Water